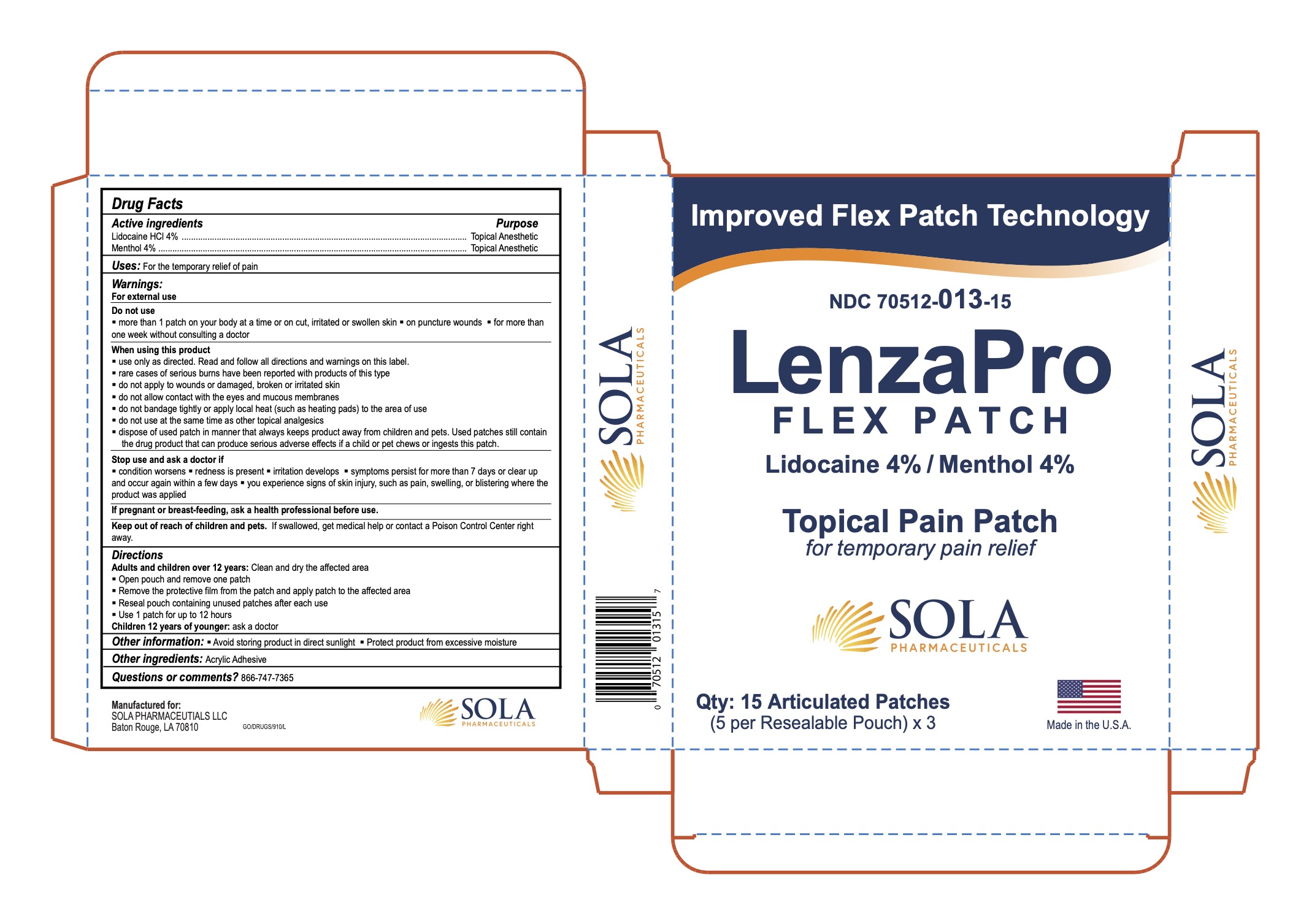 DRUG LABEL: LenzaPro Flex
NDC: 70512-013 | Form: PATCH
Manufacturer: SOLA Pharmaceuticals
Category: otc | Type: HUMAN OTC DRUG LABEL
Date: 20251208

ACTIVE INGREDIENTS: MENTHOL 40 mg/1 g; LIDOCAINE 40 mg/1 g
INACTIVE INGREDIENTS: ACRYLIC ACID

LenzaPro Flex Patch

Active ingredients:

Lidocaine HCL 4%

Menthol 4%

Purpose:

Topical Anesthetic

Uses:

For the temporary relief of pain

Warnings:

For external use

Do not use:

- More than 1 patch on your body at a time or on cut, iritated or swollen skin.
- On puncture wounds
- For more than 1 week without consulting a doctor

When using this product:

- Use only as directed. Read and follow all directions and warnings on this label.
- Rare cases of serious burns have been reported with products of this type.
- Do not apply to wounds or damaged, broken or irritated skin.
- Do not allow contact with the eyes and mucous membranes.
- Do not bandage tightly or apply local heat (such as heating pads) to the area of use.
- Do not use at the same time as other topical analgesics.
- Dispose of used patch in manner that always keeps product away from children and pets. Used patches still contain the drug product that can produce serious adverse effects if a child or pet chews or ingests this patch.

Stop use and ask a doctor if:

- Condition worsens
- Redness is present
- Irritation developes
- Symptoms persist for more than 7 days or clear up and occur again within a few days.
- You experience signs of skin injury, such as pain, swelling, or blistering where the product was applied.

PREGNANCY OR BREAST FEEDING

If pregnant or breast-feeding, ask a health care professional before use.

Keep out of reach of children and pets.

If swallowed, get medical help or contact a Poison Control Center right away.

Directions:

Adults and children over 12 years:

- Clean and dry the affected area.
- Open pouch and remove one patch.
- Remove the protective film from the patch and apply patch to the affected area.
- Reseal pouch containing unused patches after each use.
- Use 1 patch for up to 12 hours.

Children 12 years or younger:

- Ask a doctor

Other Information:

- Avoid storing product in direct sunlight
- Protect product from excessive mositure

INACTIVE INGREDIENT

Other Ingredients:

Acrylic Adhesive

Questions or comments? 866-747-7365

Manufactured For:

SOLA Pharmaceuticals LLC

Baton Rouge, LA 70810

NDC: 70512-013-15

QTY: 15 Articulated patches (5 per Resealable Pouch) x 3